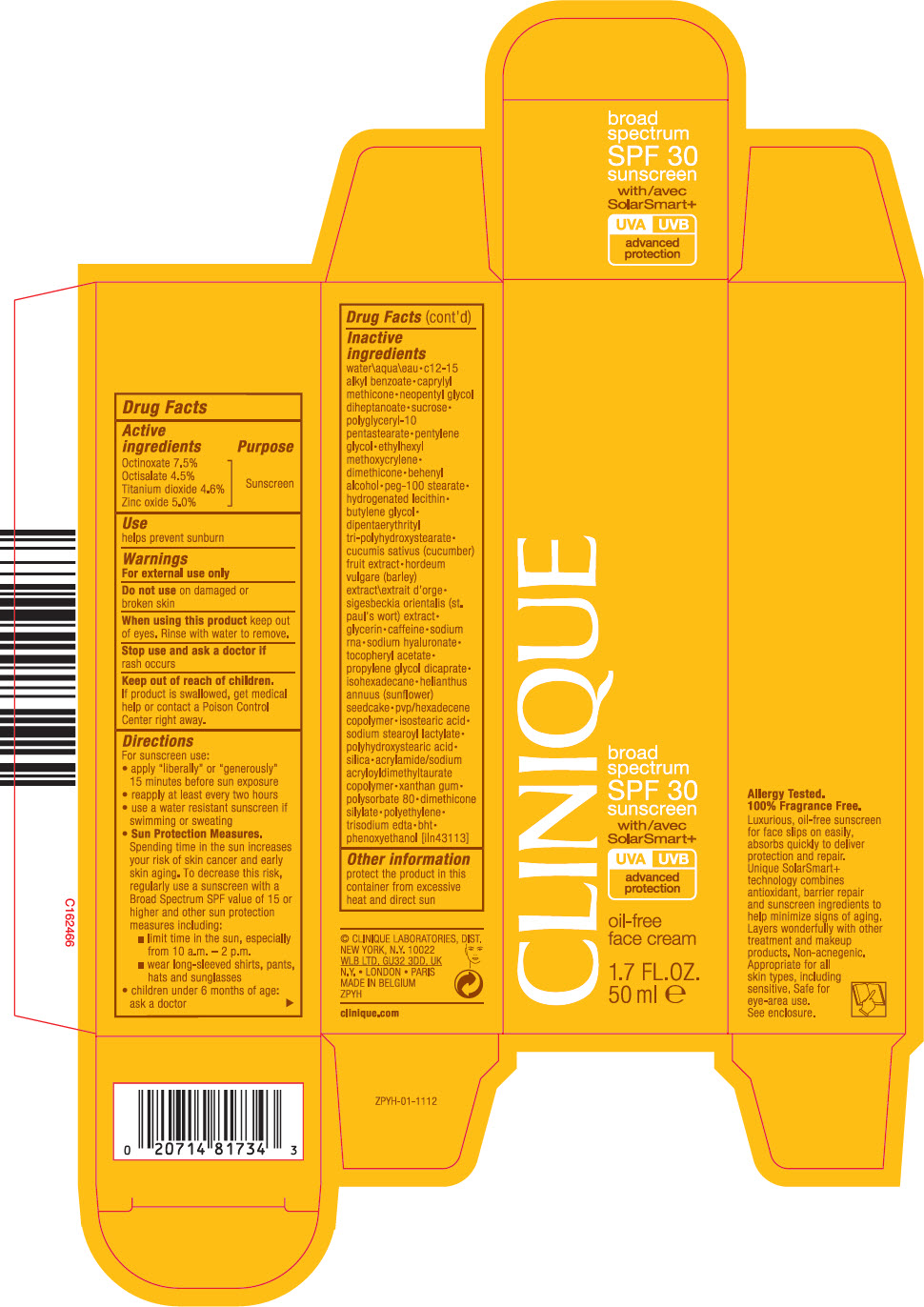 DRUG LABEL: Clinique Broad Spectrum SPF 30 Oil Free Face With Solar Smart
NDC: 49527-067 | Form: CREAM
Manufacturer: CLINIQUE LABORATORIES LLC
Category: otc | Type: HUMAN OTC DRUG LABEL
Date: 20231013

ACTIVE INGREDIENTS: OCTINOXATE 75 mg/1 mL; OCTISALATE 45 mg/1 mL; TITANIUM DIOXIDE 46 mg/1 mL; ZINC OXIDE 50 mg/1 mL
INACTIVE INGREDIENTS: WATER; ALKYL (C12-15) BENZOATE; CAPRYLYL TRISILOXANE; NEOPENTYL GLYCOL DIHEPTANOATE; SUCROSE; POLYGLYCERYL-10 PENTASTEARATE; PENTYLENE GLYCOL; ETHYLHEXYL METHOXYCRYLENE; DIMETHICONE; DOCOSANOL; PEG-100 STEARATE; HYDROGENATED SOYBEAN LECITHIN; BUTYLENE GLYCOL; DIPENTAERYTHRITYL TRI-POLYHYDROXYSTEARATE; CUCUMBER; BARLEY; GLYCERIN; CAFFEINE; HYALURONATE SODIUM; PROPYLENE GLYCOL DICAPRATE; ISOHEXADECANE; HELIANTHUS ANNUUS SEEDCAKE; ISOSTEARIC ACID; SODIUM STEAROYL LACTYLATE; SILICON DIOXIDE; XANTHAN GUM; POLYSORBATE 80; HIGH DENSITY POLYETHYLENE; EDETATE TRISODIUM; BUTYLATED HYDROXYTOLUENE; PHENOXYETHANOL

CLINIQUE BROAD SPECTRUM SPF 30 OIL FREE FACE CREAM WITH SOLAR SMART

Drug Facts

Active ingredients

Octinoxate 7.5%
Octisalate 4.5%
Titanium dioxide 4.6%
Zinc oxide 5.0%

Purpose

Sunscreen

Use

helps prevent sunburn

Warnings

For external use only

Do not use on damaged or broken skin

When using this product keep out of eyes. Rinse with water to remove.

Stop use and ask a doctor if rash occurs

Keep out of reach of children. If product is swallowed, get medical help or contact a Poison Control Center right away.

Directions

For sunscreen use:

- apply "liberally" or "generously" 15 minutes before sun exposure
- reapply at least every two hours
- use a water resistant sunscreen if swimming or sweating
- Sun Protection Measures. Spending time in the sun increases your risk of skin cancer and early skin aging. To decrease this risk, regularly use a sunscreen with a Broad Spectrum SPF value of 15 or higher and other sun protection measures including:
  - limit time in the sun, especially from 10 a.m. – 2 p.m.
  - wear long-sleeved shirts, pants, hats and sunglasses
- children under 6 months of age: ask a doctor

Inactive ingredients

water\aqua\eau • c12-15 alkyl benzoate • caprylyl methicone • neopentyl glycol diheptanoate • sucrose • polyglyceryl-10 pentastearate • pentylene glycol • ethylhexyl methoxycrylene • dimethicone • behenyl alcohol • peg-100 stearate • hydrogenated lecithin • butylene glycol • dipentaerythrityl tri-polyhydroxystearate • cucumis sativus (cucumber) fruit extract • hordeum vulgare (barley) extract\extrait d'orge • sigesbeckia orientalis (st. paul's wort) extract • glycerin • caffeine • sodium rna • sodium hyaluronate • tocopheryl acetate • propylene glycol dicaprate • isohexadecane • helianthus annuus (sunflower) seedcake • pvp/hexadecene copolymer • isostearic acid • sodium stearoyl lactylate • polyhydroxystearic acid • silica • acrylamide/sodium acryloyldimethyltaurate copolymer • xanthan gum • polysorbate 80 • dimethicone silylate • polyethylene • trisodium edta • bht • phenoxyethanol [iln43113]

Other information

protect the product in this container from excessive heat and direct sun

PRINCIPAL DISPLAY PANEL - 50 ml Tube Carton

CLINIQUE

broad
spectrum
SPF 30
sunscreen
with
SolarSmart+
UVA UVB
advanced
protection

oil-free
face cream

1.7 FL. OZ.
50 ml e